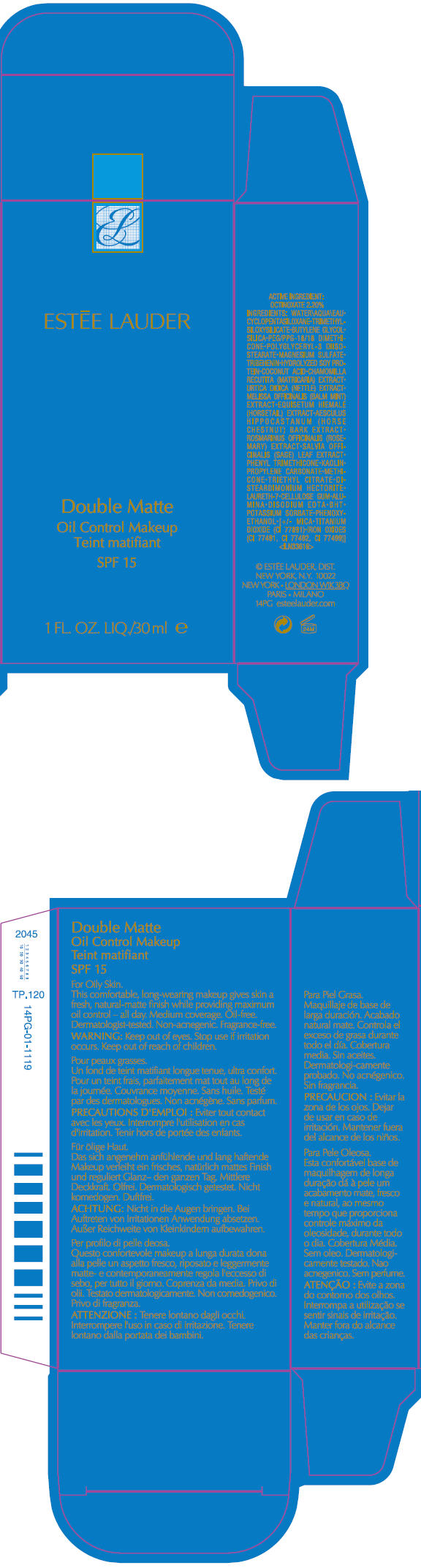 DRUG LABEL: DOUBLE MATTE 
NDC: 11559-732 | Form: LIQUID
Manufacturer: Estee Lauder Inc.
Category: otc | Type: HUMAN OTC DRUG LABEL
Date: 20111029

ACTIVE INGREDIENTS: OCTINOXATE 2.2 mL/100 mL
INACTIVE INGREDIENTS: WATER; CYCLOMETHICONE 5; BUTYLENE GLYCOL; SILICON DIOXIDE; MAGNESIUM SULFATE, UNSPECIFIED; TRIBEHENIN; COCONUT ACID; MATRICARIA RECUTITA; URTICA DIOICA LEAF; MELISSA OFFICINALIS; EQUISETUM HYEMALE; AESCULUS HIPPOCASTANUM BARK; ROSEMARY; SAGE; PHENYL TRIMETHICONE; KAOLIN; PROPYLENE CARBONATE; TRIETHYL CITRATE; LAURETH-7; CARBOXYMETHYLCELLULOSE SODIUM; ALUMINUM OXIDE; EDETATE DISODIUM; BUTYLATED HYDROXYTOLUENE; POTASSIUM SORBATE; PHENOXYETHANOL; MICA; TITANIUM DIOXIDE; FERRIC OXIDE RED; FERRIC OXIDE YELLOW; FERROSOFERRIC OXIDE

Double Matte
Oil Control Makeup
SPF 15

ACTIVE INGREDIENT

OCTINOXATE 2.20%

INGREDIENTS

WATER•CYCLOPENTASILOXANE•TRIMETHYLSILOXYSILICATE•BUTYLENE GLYCOL•SILICA•PEG/PPG-18/18 DIMETHICONE•POLYGLYCERYL-3 DIISOSTEARATE•MAGNESIUM SULFATE•TRIBEHENIN•HYDROLYZED SOY PROTEIN•COCONUT ACID•CHAMOMILLA RECUTITA (MATRICARIA) EXTRACT• URTICA DIOICA (NETTLE) EXTRACT•MELISSA OFFICINALIS (BALM MINT) EXTRACT•EQUISETUM HIEMALE (HORSETAIL) EXTRACT•AESCULUS HIPPOCASTANUM (HORSE CHESTNUT) BARK EXTRACT•ROSMARINUS OFFICINALIS (ROSEMARY) EXTRACT•SALVIA OFFICINALIS (SAGE) LEAF EXTRACT•PHENYL TRIMETHICONE•KAOLIN•PROPYLENE CARBONATE•METHICONE•TRIETHYL CITRATE•DISTEARDIMONIUM HECTORITE•LAURETH-7•CELLULOSE GUM•ALUMINA•DISODIUM EDTA•BHT•POTASSIUM SORBATE•PHENOXYETHANOL•[+/- MICA•TITANIUM DIOXIDE (CI 77891)•IRON OXIDES (CI 77491, CI 77492, CI 77499)]

© ESTĒE LAUDER, DIST.
NEW YORK, N.Y. 10022

WARNING

WHEN USING

Keep out of eyes.

Stop use if irritation occurs.

Keep out of reach of children.

PRINCIPAL DISPLAY PANEL - 30 ml Carton

ESTĒE LAUDER

Double Matte
Oil Control Makeup
SPF 15

1 FL. OZ. LIQ./30 ml e